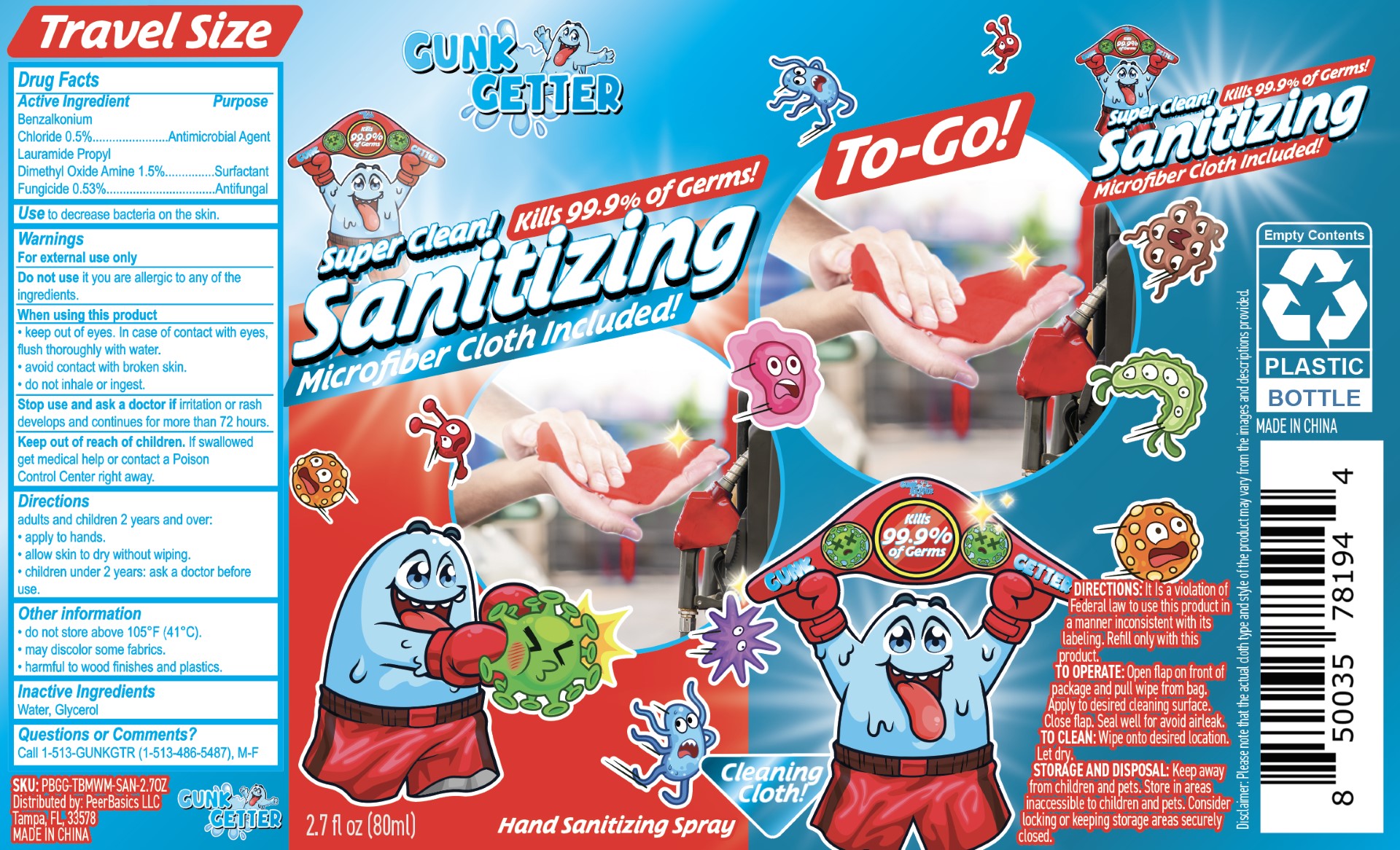 DRUG LABEL: Gunk Getter Sanitizing
NDC: 83590-002 | Form: SPRAY
Manufacturer: PeerBasics LLC
Category: otc | Type: HUMAN OTC DRUG LABEL
Date: 20230824

ACTIVE INGREDIENTS: LAURAMIDOPROPYLAMINE OXIDE 1.5 mg/100 mL; BENZALKONIUM CHLORIDE 0.5 mg/100 mL
INACTIVE INGREDIENTS: TRIETHOXYSILYLPROPYL STEARDIMONIUM CHLORIDE; WATER; GLYCERIN

Active Ingredient

Benzalkonium Chloride

Lauramide Propyl Dimethyl Oxide Amine

Purpose

Antimicrobial Agent

Surfactant

Antifugal

Use

Use to decrase bacteria on the skin.

Warnings

For external use only

Do not use it you are allergic to any of the ingredients.

When using this product

- keep out of eyes. In case of contact with eyes, flush thoroughly with water.
- avoid contact with broken skin.
- do not inhale or ingest.

Stop use and ask a doctor if

irritation or rash develops and continues for more than72 hours.

Keep out of reach of children.

If swallowed, get medical help or contact a Poison Control Center right away.

Directions

adults and children 2 years and over:

- apply to hands.
- allow skin to dry without wiping.
- children under 2 years: ask a doctor before use.

Other information

- do not store above 105F(41C).
- may discolor some fabrics.
- harmful to wood finishes and plastics.

Inactive Ingredients

Water

Glycerol

Fungicide